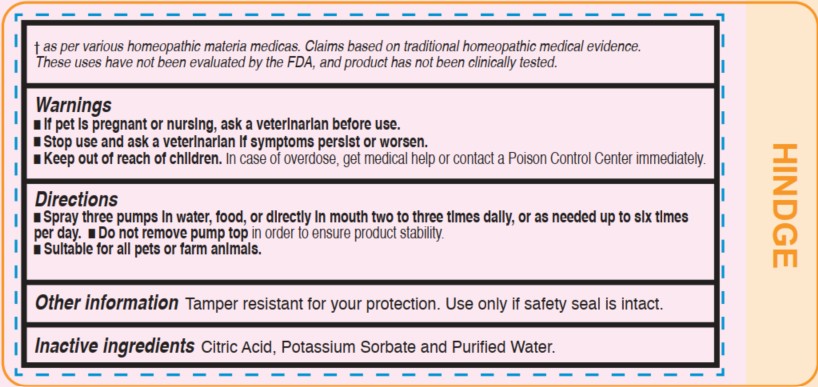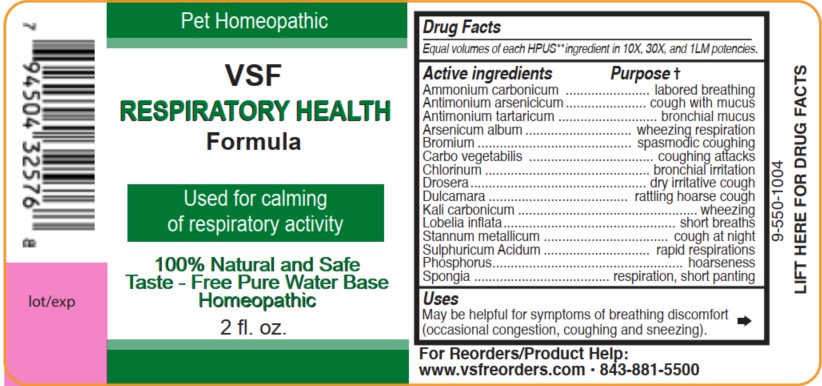 DRUG LABEL: Respiratory Health Formula
NDC: 86100-0014 | Form: LIQUID
Manufacturer: Vsf2 Inc.
Category: homeopathic | Type: OTC ANIMAL DRUG LABEL
Date: 20250812

ACTIVE INGREDIENTS: AMMONIUM CARBONATE 10 [hp_X]/59 mL; ANTIMONY ARSENATE 10 [hp_X]/59 mL; ANTIMONY POTASSIUM TARTRATE 10 [hp_X]/59 mL; ARSENIC TRIOXIDE 10 [hp_X]/59 mL; BROMINE 10 [hp_X]/59 mL; ACTIVATED CHARCOAL 10 [hp_X]/59 mL; CHLORINE 10 [hp_X]/59 mL; DROSERA ROTUNDIFOLIA WHOLE 10 [hp_X]/59 mL; SOLANUM DULCAMARA TOP 10 [hp_X]/59 mL; POTASSIUM CARBONATE 10 [hp_X]/59 mL; LOBELIA INFLATA WHOLE 10 [hp_X]/59 mL; TIN 10 [hp_X]/59 mL; SULFURIC ACID 10 [hp_X]/59 mL; PHOSPHORUS 10 [hp_X]/59 mL; SPONGIA OFFICINALIS SKELETON, ROASTED 10 [hp_X]/59 mL
INACTIVE INGREDIENTS: ANHYDROUS CITRIC ACID; POTASSIUM SORBATE; WATER

Respiratory Health Formula

Active ingredients

Equal volumes of each HPUS** ingredient in 10X,
30X, and 1LM potencies.

Ammonium carbonicum, Antimonium arsenicicum, Antimonium tartaricum, Arsenicum album, Bromium, Carbo vegetabilis, Chlorinum, Drosera, Dulcamara, Kali carbonicum, Lobelia inflata, Stannum metallicum, Sulphuricum acidum, Phosphorus, and Spongia.

As per various homeopathic materia medicas. Claims based on traditional homeopathic medical evidence.

These uses have not been evaluated by the FDA, and product has not been clinically tested.

Uses

May be helpful for symptoms of breathing discomfort (occasional congestion, coughing and sneezing).

Questions

VSF Respiratory Health Formula 2fl oz.

100% Natural and Safe Taste

Free Pure Water Base

Pet Homeopathic

For reorders/Product Help:

www.vsfreorders.com 843-881-5500

Warnings

- If pet is pregnant or nursing, ask a veterinarian before use.
- Stop use and ask a veterinarian if symptoms persist or worsen.
- Keep out of reach of children. In case of overdose, get medical help or contact a Poison Control Center immediately.

Keep out of reach of children.

In case of overdose, get medical help or contact a Poison Control Center immediately.

Directions

- Spray three pumps in water, food, or directly in mouth two to three times daily, or as needed up to six times per day.
- Do not remove pump top in order to ensure product stability.
- Suitable for all pets or farm animals.

Other information

Tamper resistant for your protection.

Use only if safety seal is intact.

Inactive Ingredients

Citric Acid, Potassium Sorbate, and Purified Water.

PURPOSE

Equal volumes of each HPUS** ingredient in 10X,
30X, and 1LM potencies.

Active ingredients Purpose †

Ammonium carbonicum.................................labored breathing

Antimonium arsenicicum...............................cough with mucus

Antimonium tartaricum...................................bronchial mucus

Arsenicum album.....................................wheezing respiration

Bromium.................................................spasmodic coughing

Carbo vegetabilis..........................................coughing attacks

Chlorinum..................................................bronchial irritation

Drosera....................................................dry irritative cough

Dulcamara.............................................rattling hoarse cough

Kali carbonicum......................................................wheezing

Lobelia inflata...................................................short breaths

Stannum metallicum........................................cough at night

Sulphuricum acidum....................................rapid respirations

Phosphorus.........................................................hoarseness

Spongia..........................................respiration, short panting

As per various homeopathic materia medicas. Claims based on traditional homeopathic medical evidence.

These uses have not been evaluated by the FDA, and product has not been clinically tested.